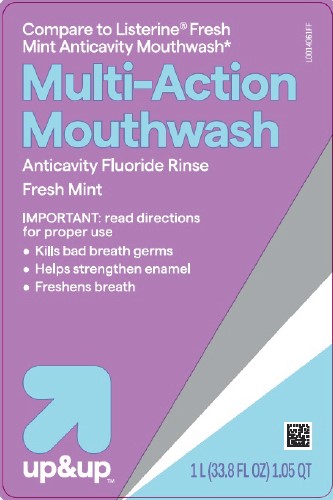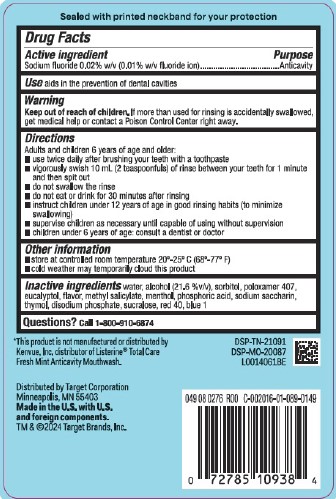 DRUG LABEL: Anticavity Fluoride Rinse
NDC: 11673-163 | Form: MOUTHWASH
Manufacturer: Target Corporation
Category: otc | Type: HUMAN OTC DRUG LABEL
Date: 20260218

ACTIVE INGREDIENTS: SODIUM FLUORIDE 0.1 mg/1 mL
INACTIVE INGREDIENTS: WATER; ALCOHOL; SORBITOL; POLOXAMER 407; EUCALYPTOL; METHYL SALICYLATE; MENTHOL; PHOSPHORIC ACID; SACCHARIN SODIUM; THYMOL; SODIUM PHOSPHATE, DIBASIC, ANHYDROUS; SUCRALOSE; FD&C RED NO. 40; FD&C BLUE NO. 1

Up & Up 163.005/163AF-AG
Anticavity Fluoride Rinse

Tamper Evident Statement

Sealed with printed neckband for your protection

Active ingredient

Sodium fluoride 0.02% w/v (0.01% w/v fluoride ion)

Purpose

Anticavity

Use

aids in the prevention of dental cavities

Warning

for this product

Keep out of reach of children.

If more than used for rinsing is accidentally swallowed, get medical help or contact a Poison Control Center right away.

Directions

Adults and children 6 years of age and older:

- use twice daily after brushing your teeth with toothpaste
- vigorously swish 10 mL (2 teaspoonfuls) of rinse between your teeth for 1 minute and then spit out
- do not swallow the rinse
- do not eat or drink for 30 minutes after rinsing
- instruct children under 12 years of age in good rinsing habits (to minimize swallowing)
- supervise children as necessary until capable of using without supervision
- children under 6 years of age: consult a dentist or doctor

Other information

- store at controlled room temperature 20⁰-25⁰ C (68⁰ - 77⁰ F)
- cold weather may temporarily cloud this product

Inactive ingredients

water, alcohol (21.6 %v/v), sorbitol, poloxamer 407, eucalyptol, flavor, methyl salicylate, menthol, phosphoric acid, sodium saccharin, thymol, disodium phosphate, sucralose, red 40, blue 1

Questions?

Call 1-800-910-6874

Disclaimer

*This product is not manufactured or distributed by Kenvue, Inc. distributor of Listerine®Total Care Fresh Mint Anticavity Mouthwash.

Adverse reaction

Distributed by Target Corporation

Minneapolis, MN 55403

Made in the U.S. with U.S. and foreign components.

TM & ©2024 Target Brands, Inc.

DSP-TN-21091

DSP-MO-20087

Principal Panel Display

Compare to Listerine®Fresh Mint Anticavity Mouthwash*

Multi-Action

Mouthwash

Anticavity Fluoride Rinse

Fresh Mint

IMPORTANT: read directions for proper use

- Kills bad breath germs
- Helps strengthen enamel
- Freshens breath

up&up™

1 L (33.8 FL OZ) 1.05 QT